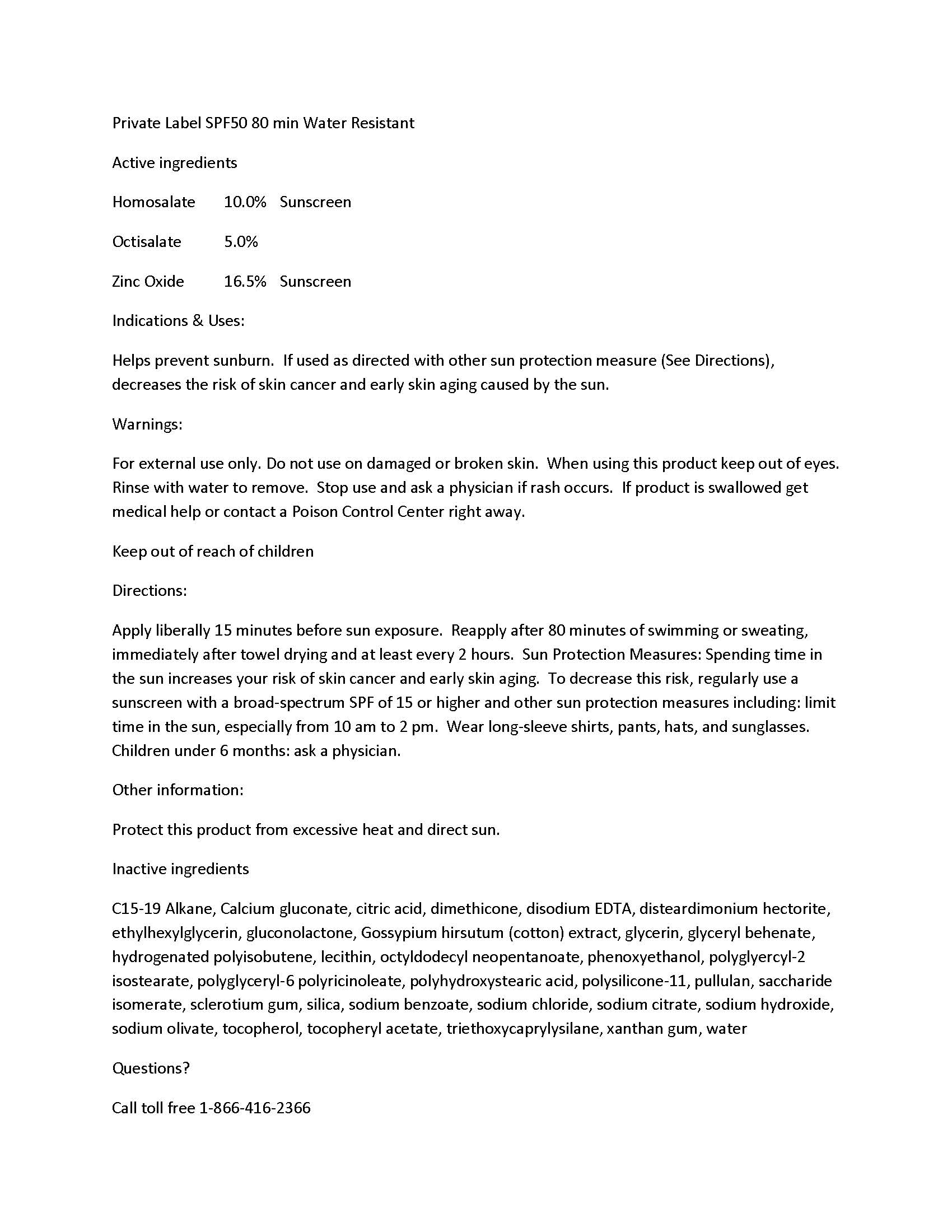 DRUG LABEL: Private Label SPF 50 80 min Water Resistant
NDC: 60232-0035 | Form: CREAM
Manufacturer: Swiss-American CDMO, LLC
Category: otc | Type: HUMAN OTC DRUG LABEL
Date: 20231114

ACTIVE INGREDIENTS: HOMOSALATE 100 g/1000 g; OCTISALATE 50 g/1000 g; ZINC OXIDE 165 g/1000 g
INACTIVE INGREDIENTS: WATER; SODIUM HYDROXIDE; EDETATE DISODIUM; GLYCERIN; SODIUM CHLORIDE; PHENOXYETHANOL; ETHYLHEXYLGLYCERIN; OCTYLDODECYL NEOPENTANOATE; C15-19 ALKANE; POLYHYDROXYSTEARIC ACID (2300 MW); TRIETHOXYCAPRYLYLSILANE; SORBITAN OLIVATE; DIMETHICONE; TOCOPHEROL; DISTEARDIMONIUM HECTORITE; POLYGLYCERYL-2 ISOSTEARATE; POLYGLYCERYL-6 POLYRICINOLEATE; GLUCONOLACTONE; SODIUM BENZOATE; CALCIUM GLUCONATE; SACCHARIDE ISOMERATE; CITRIC ACID MONOHYDRATE; SODIUM CITRATE; HYDROGENATED POLYBUTENE (1300 MW); GOSSYPIUM HIRSUTUM LEAF; GLYCERYL MONOBEHENATE; .ALPHA.-TOCOPHEROL ACETATE; XANTHAN GUM; LECITHIN, SOYBEAN; PULLULAN; BETASIZOFIRAN; SILICON DIOXIDE; DIMETHICONE/VINYL DIMETHICONE CROSSPOLYMER (SOFT PARTICLE)

Private Label SPF 50 80 min Water Resistant

Warnings

For external use only. Do not use on damaged or broken skin. When using this product keep out of eyes. Rinse with water to remove. Stop use and ask a physician if rash occurs. If product is swallowed get medical help or contact a Poison Control Center right away.

Uses

Helps prevent sunburn. If used as directed with other sun protection measure (See Directions), decreases the risk of skin cancer and early skin aging caused by the sun.

Uses

Helps prevent sunburn. If used as directed with other sun protection measure (See Directions), decreases the risk of skin cancer and early skin aging caused by the sun.

KEEP OUT OF REACH OF CHILDREN

Active Ingredients

Homosalate 10.0% Sunscreen
Octisalate 5.0%
Zinc Oxide 16.5% Sunscreen

Directions

Apply liberally 15 minutes before sun exposure. Reapply after 80 minutes of swimming or sweating, immediately after towel drying and at least every 2 hours. Sun Protection Measures: Spending time in the sun increases your risk of skin cancer and early skin aging. To decrease this risk, regularly use a sunscreen with a broad-spectrum SPF of 15 or higher and other sun protection measures including: limit time in the sun, especially from 10 am to 2 pm. Wear long-sleeve shirts, pants, hats, and sunglasses. Children under 6 months: ask a physician.

Other safety information

Protect this product from excessive heat and direct sun.

Inactive Ingredients

C15-19 Alkane, Calcium gluconate, citric acid, dimethicone, disodium EDTA, disteardimonium hectorite, ethylhexylglycerin, gluconolactone, Gossypium hirsutum (cotton) extract, glycerin, glyceryl behenate, hydrogenated polyisobutene, lecithin, octyldodecyl neopentanoate, phenoxyethanol, polyglyercyl-2 isostearate, polyglyceryl-6 polyricinoleate, polyhydroxystearic acid, polysilicone-11, pullulan, saccharide isomerate, sclerotium gum, silica, sodium benzoate, sodium chloride, sodium citrate, sodium hydroxide, sodium olivate, tocopherol, tocopheryl acetate, triethoxycaprylysilane, xanthan gum, water

Questions?

Call toll free 1-866-416-2366